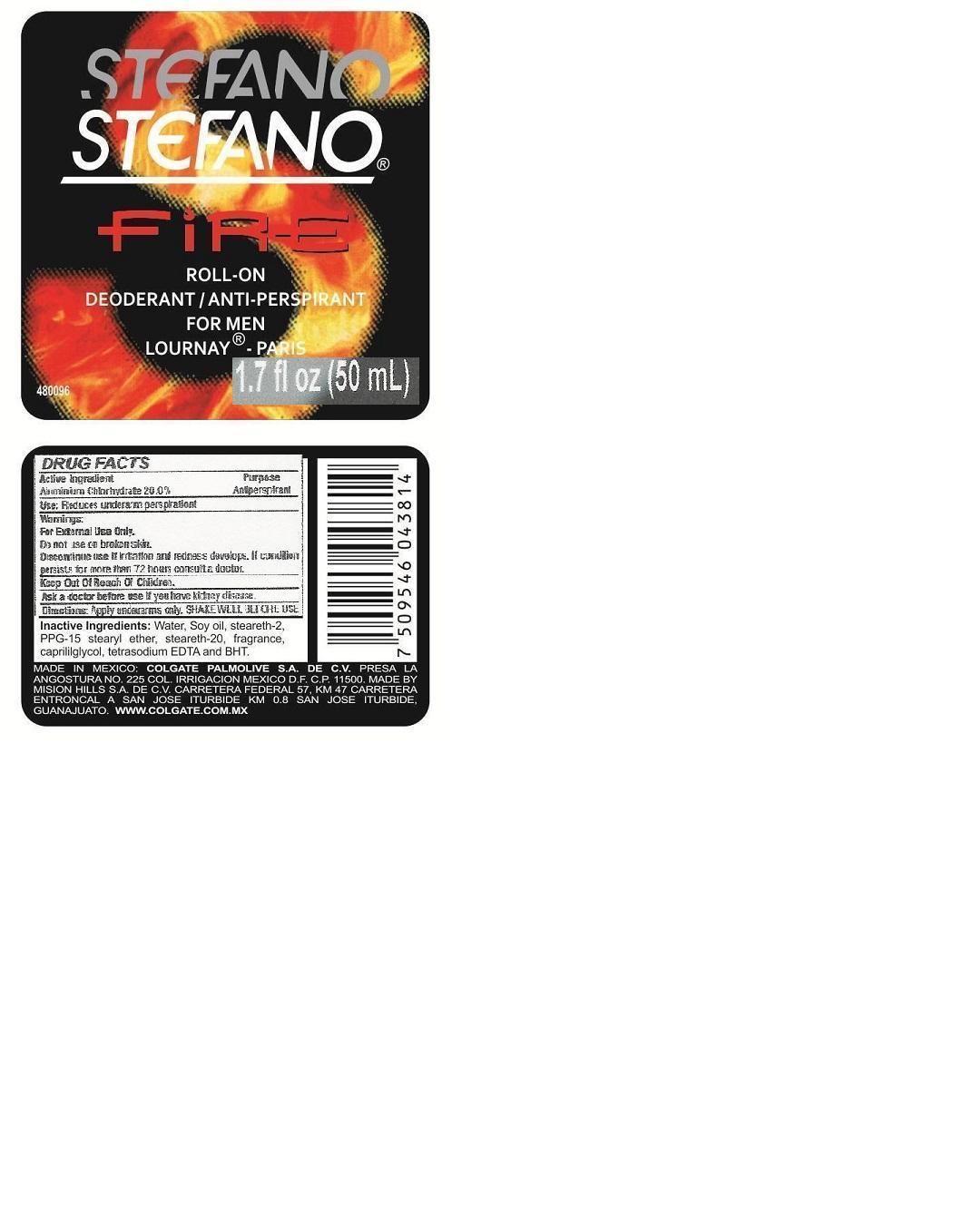 DRUG LABEL: Stefano
NDC: 69772-980 | Form: LIQUID
Manufacturer: Teresa Cecena DBA Genesis
Category: otc | Type: HUMAN OTC DRUG LABEL
Date: 20150518

ACTIVE INGREDIENTS: ALUMINUM CHLOROHYDRATE 25 g/100 mL
INACTIVE INGREDIENTS: WATER; STEARETH-2; PPG-15 STEARYL ETHER; STEARETH-20; EDETATE SODIUM; BUTYLATED HYDROXYTOLUENE; CAPRYLYL GLYCOL

ACTIVE INGREDIENT

Aluminum Chlorohydrate

Purpose

Antiperspirant

KEEP OUT OF THE REACH OF CHILDREN

Use

Reduces underarm persperation.

Directions:

Apply under arm only

SHAKE WELL BEFORE USE

WARNINGS

FOR EXTERNAL USE ONLY

Do not apply on irrited or injured skin. Discontinue use if you experience some irritation, redness or discomfort

INACTIVE INGREDIENT

Water, soy oil, stearth-2, PPG-15 Stearyl ether, steareth-20, fragance, caprylyl glycol, tetrasodium, EDTA, and BHT

DOSAGE AND ADMINISTRATION

For External Use Only

Apply under arm only